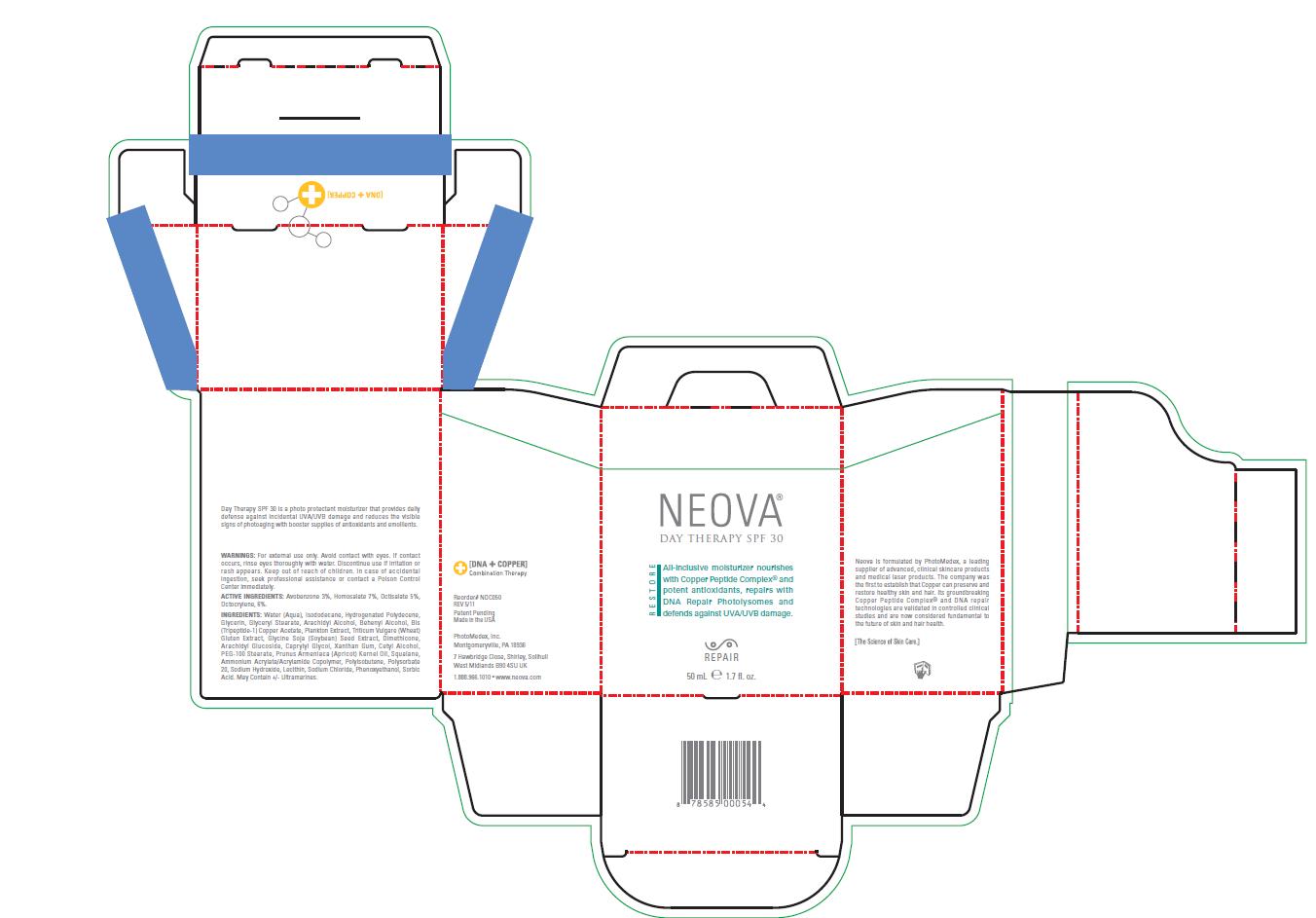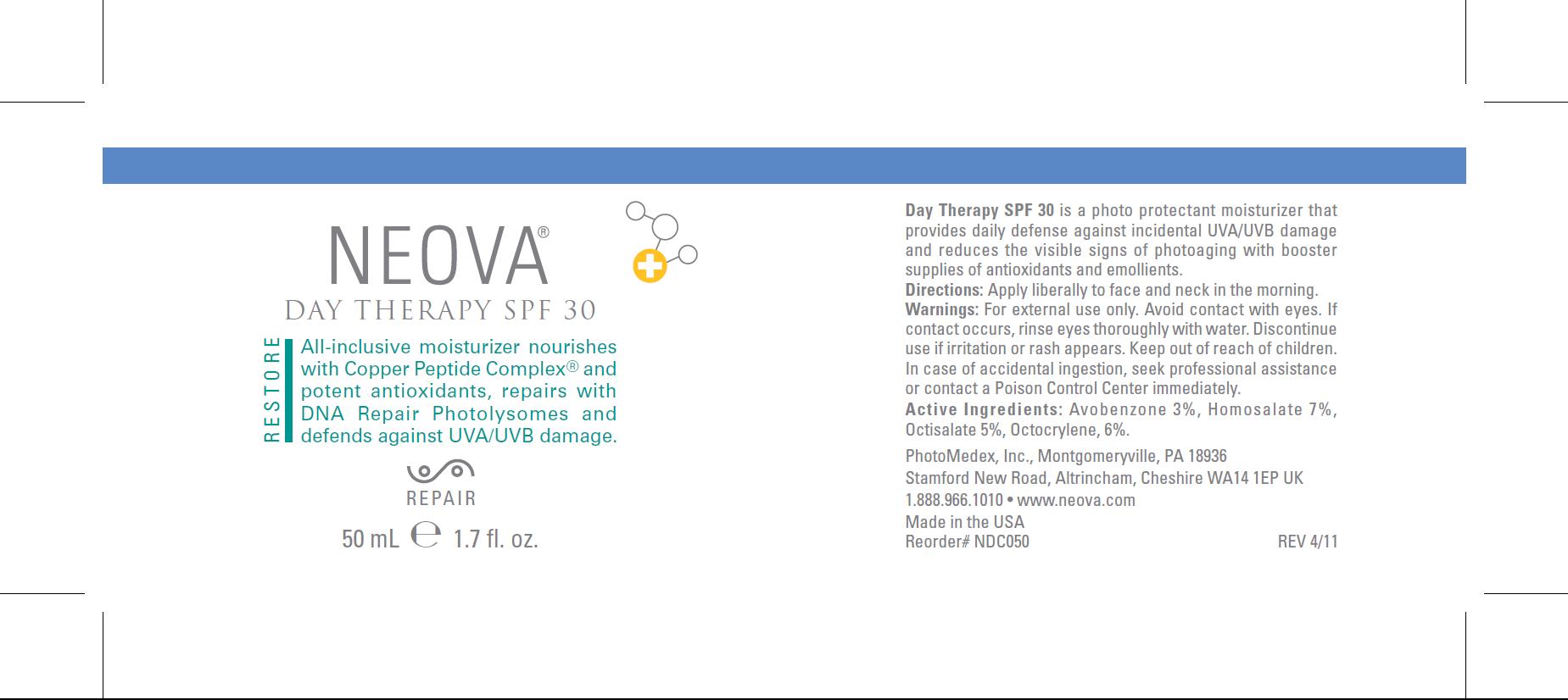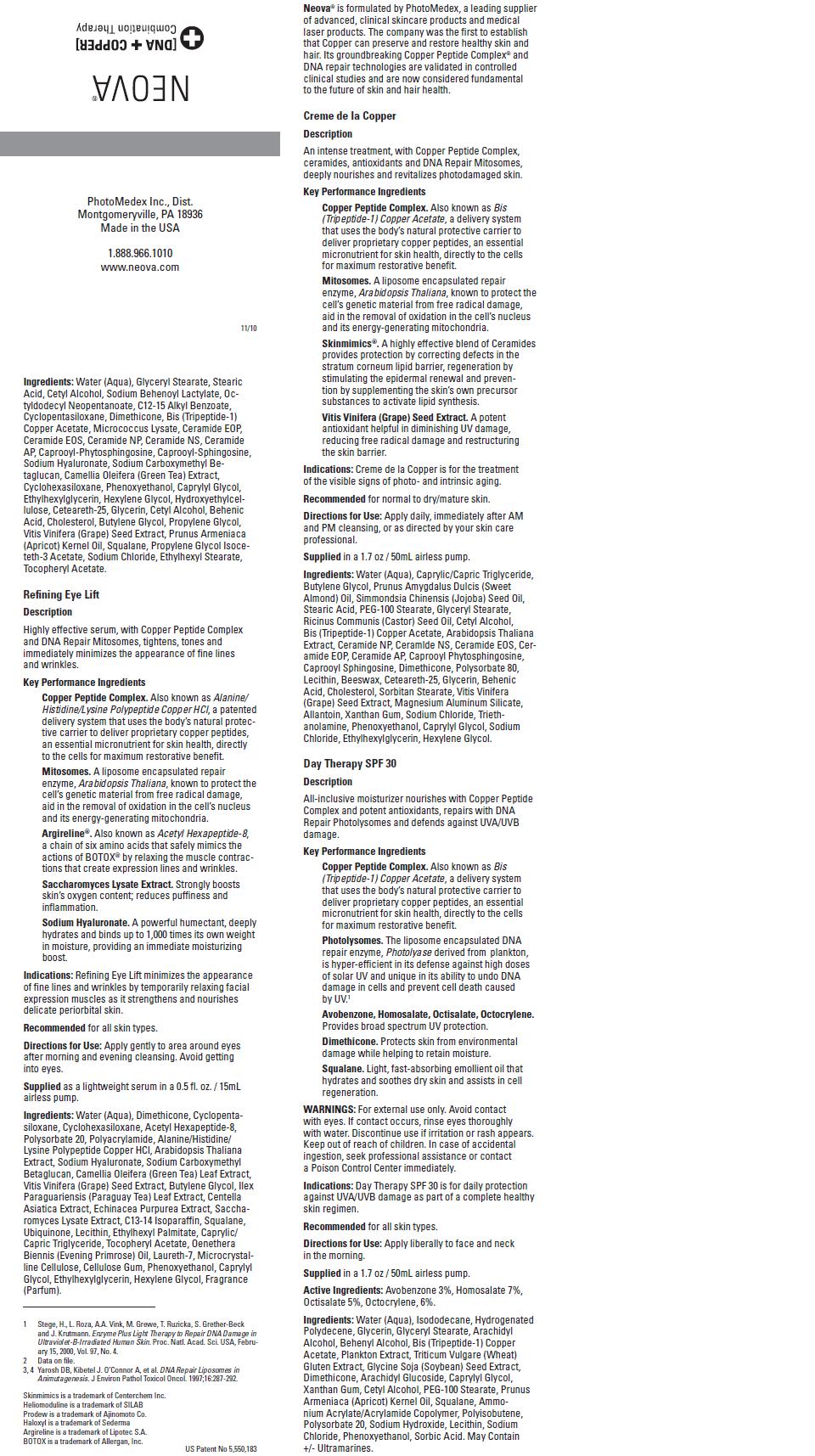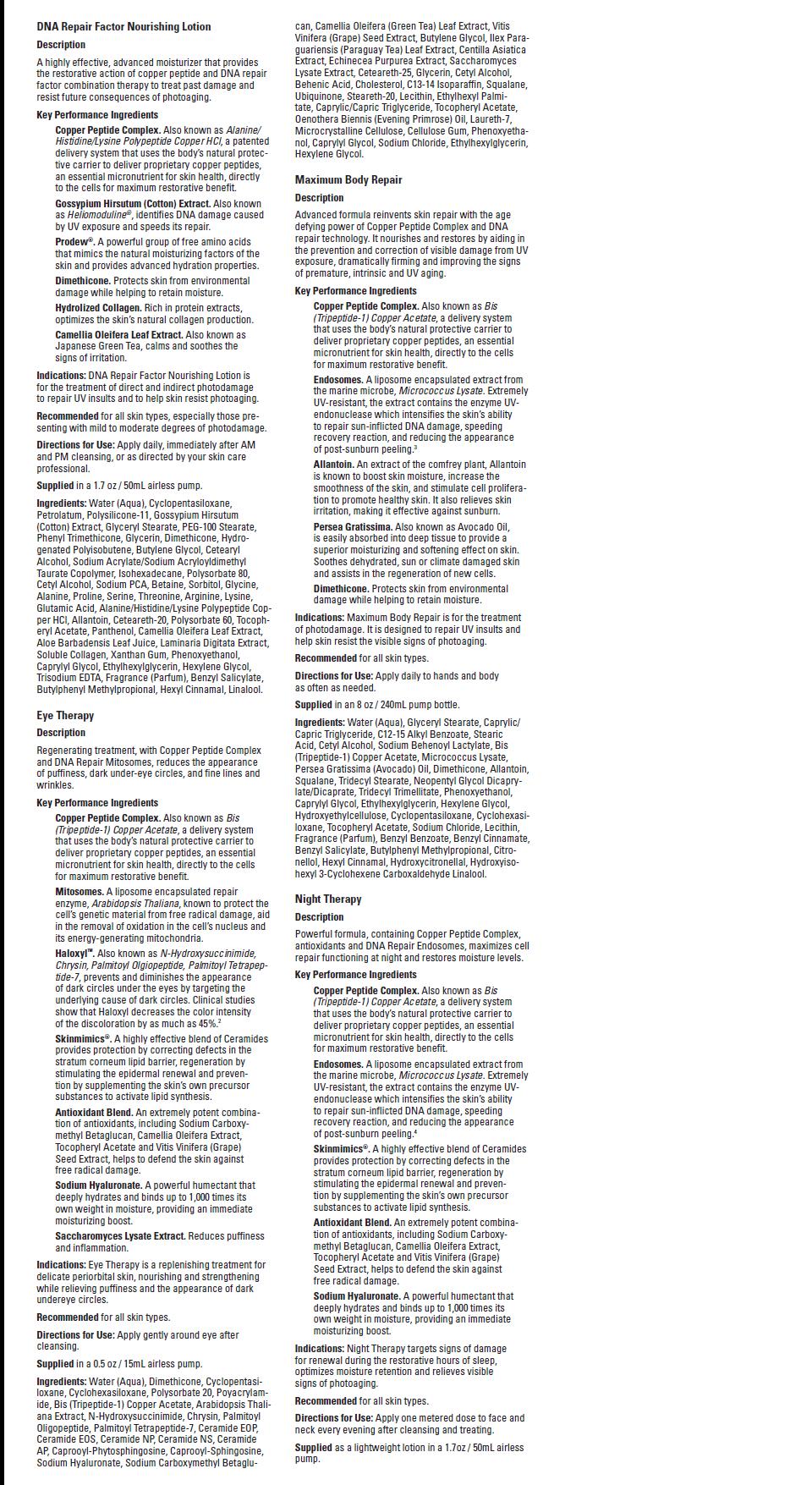 DRUG LABEL: Neova Day Therapy
NDC: 62362-184 | Form: LOTION
Manufacturer: PhotoMedex, Inc.
Category: otc | Type: HUMAN OTC DRUG LABEL
Date: 20120111

ACTIVE INGREDIENTS: Homosalate 7 mL/100 mL; Octocrylene 6 mL/100 mL; Octisalate 5 mL/100 mL; Avobenzone 3 mL/100 mL
INACTIVE INGREDIENTS: Water; Isododecane; Hydrogenated Polydecene (550 MW); Glycerin; Glyceryl Monostearate; Arachidyl Alcohol; Docosanol; Prezatide Copper Acetate; Soybean; Dimethicone; Arachidyl Glucoside; Caprylyl Glycol; Xanthan Gum; Cetyl Alcohol; PEG-100 Stearate; Apricot Kernel Oil; Squalane; Polyisobutylene (1300 MW); Polysorbate 20; Sodium Hydroxide ; Lecithin, Soybean; Sodium Chloride; Phenoxyethanol; Sorbic Acid

Neova - Day Therapy - SPF 30 - 50mL - 1.7 fl. oz.

Warnings

For external use only. Avoid contact with eyes. If contact
occurs, rinse eyes thoroughly with water. Discontinue use if irritation or
rash appears. Keep out of reach of children. In case of accidental
ingestion, seek professional assistance or contact a Poison Control
Center immediately.

Active Ingredients

Avobenzone 3%, Homosalate 7%, Octisalate 5%,
Octocrylene, 6%.

Inactive Ingredients

Water (Aqua), Isododecane, Hydrogenated Polydecene,
Glycerin, Glyceryl Stearate, Arachidyl Alcohol, Behenyl Alcohol, Bis
(Tripeptide-1) Copper Acetate, Plankton Extract, Triticum Vulgare (Wheat)
Gluten Extract, Glycine Soja (Soybean) Seed Extract, Dimethicone,
Arachidyl Glucoside, Caprylyl Glycol, Xanthan Gum, Cetyl Alcohol,
PEG-100 Stearate, Prunus Armeniaca (Apricot) Kernel Oil, Squalane,
Ammonium Acrylate/Acrylamide Copolymer, Polyisobutene, Polysorbate
20, Sodium Hydroxide, Lecithin, Sodium Chloride, Phenoxyethanol, Sorbic
Acid. May Contain +/- Ultramarines.

Image of Package Insert, box, and label

PkgInsertComboTherapypg1.jpg PkgInsertComboTherapypg2.jpg DayTherapy50mLImpt.jpg DayTherapy50mLBox.jpg